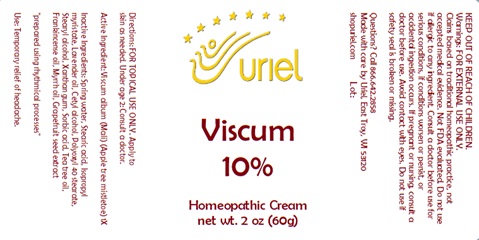 DRUG LABEL: Viscum 10
NDC: 48951-9050 | Form: CREAM
Manufacturer: Uriel Pharmacy Inc.
Category: homeopathic | Type: HUMAN OTC DRUG LABEL
Date: 20240326

ACTIVE INGREDIENTS: VISCUM ALBUM FRUITING TOP 1 [hp_X]/1 g
INACTIVE INGREDIENTS: WATER; STEARIC ACID; ISOPROPYL MYRISTATE; LAVENDER OIL; CETYL ALCOHOL; POLYOXYL 40 STEARATE; STEARYL ALCOHOL; XANTHAN GUM; SORBIC ACID; FRANKINCENSE OIL; MYRRH OIL; CITRUS PARADISI SEED; TEA TREE OIL

Viscum 10

INDICATIONS AND USAGE

Directions: FOR TOPICAL USE ONLY.

DOSAGE AND ADMINISTRATION

Apply to skin as needed. Under age 2: Consult a doctor.

Active Ingredient: Viscum album (Mali) (Apple tree mistletoe) 1X

INACTIVE INGREDIENT

Inactive Ingredients: Spring water, Stearic acid, Isopropyl myristate, Lavender oil, Cetyl alcohol, Polyoxyl 40 stearate, Stearyl alcohol, Xanthan gum, Sorbic acid, Tea tree oil, Frankincense oil, Myrrh oil, Grapefruit seed extract

prepared using rhythmical processes

PURPOSE

Use: Temporary relief of headache

KEEP OUT OF REACH OF CHILDREN.

WARNINGS

Warnings: FOR EXTERNAL USE ONLY. Do not use if allergic to any ingredient. Consult a doctor before use for serious conditions, if conditions worsen or persist, or accidental ingestion occurs. If pregnant or nursing, consult a doctor before use. Avoid contact with eyes. Do not use if safety seal is broken or missing.

QUESTIONS

Questions? Call 866.642.2858 Made with care by Uriel, East Troy, WI 53120 shopuriel.com Lot: